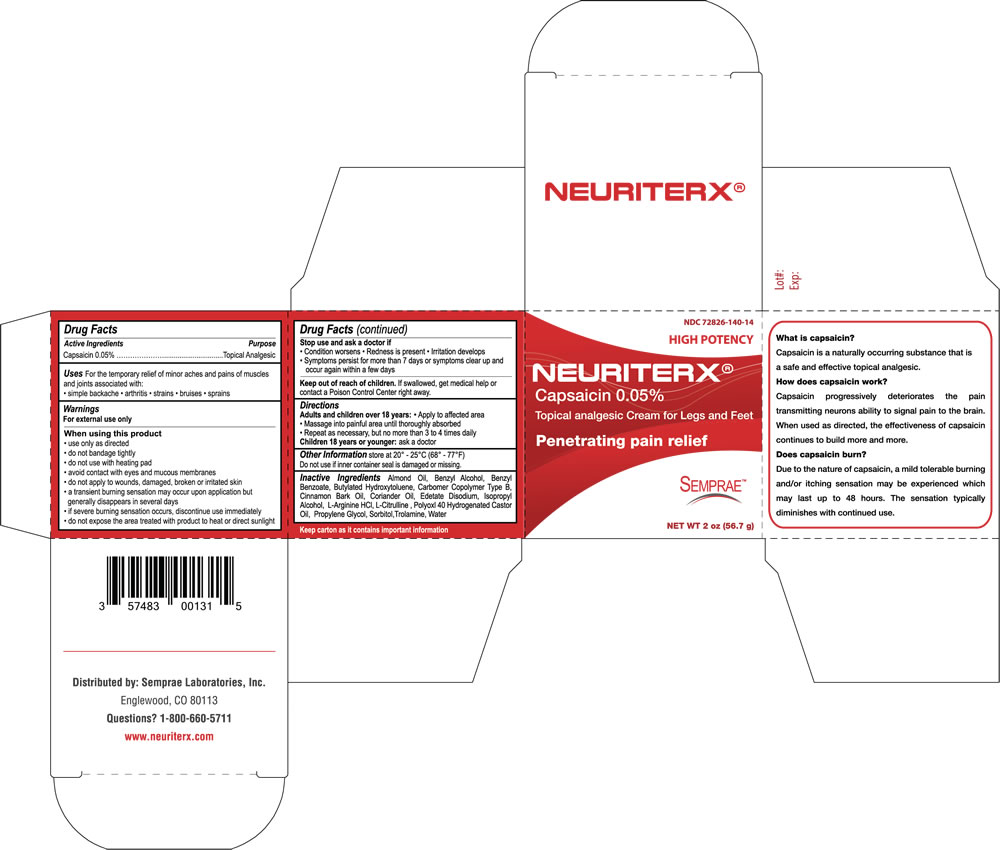 DRUG LABEL: Neuriterx
NDC: 72826-140 | Form: CREAM
Manufacturer: Semprae Laboratories Inc
Category: otc | Type: HUMAN OTC DRUG LABEL
Date: 20201120

ACTIVE INGREDIENTS: CAPSAICIN .05 g/100 g
INACTIVE INGREDIENTS: ALMOND OIL; BENZYL ALCOHOL; BENZYL BENZOATE; BUTYLATED HYDROXYTOLUENE; CARBOMER COPOLYMER TYPE B (ALLYL PENTAERYTHRITOL CROSSLINKED); CINNAMON BARK OIL; CORIANDER OIL; EDETATE DISODIUM; ISOPROPYL ALCOHOL; ARGININE HYDROCHLORIDE; CITRULLINE; POLYOXYL 40 HYDROGENATED CASTOR OIL; PROPYLENE GLYCOL; SORBITOL; TROLAMINE; WATER

Capsaicin

Active Ingredient

Capsaicin 0.05%

Purpose

Topical analgesic

Uses

For the temporary relief of minor aches and pains of muscles and joints due to

- simple backache
- arthritis
- strains
- sprains

Warnings

For external use only

When using this product

• use only as directed
• do not bandage tightly
• do not use with heating pad
• avoid contact with eyes and mucous membranes
• do not apply to wounds, damaged, broken or irritated skin
• a transient burning sensation may occur upon application but generally disappears in several days
• if severe burning sensation occurs, discontinue use immediately
• do not expose the area treated with product to heat or direct sunlight

Stop use and ask a doctor if

- Condition worsens
- Redness is present
- Irritation develops
- Symptoms persist for more than 7 days or symptoms clear up and occur again within a few days

Keep out of reach of children

If swallowed, get medical help or contact a Poison Control Center right away.

Directions

Adults and children over 18 years:

- Apply to affected area
- Massage into painful area until thoroughly absorbed
- Repeat as necessary, but no more than 3 to 4 times daily

Children 18 years or younger: ask a doctor

Other Information

Store at 20° - 25°C (68° - 77°F)
Do not use if inner container seal is damaged or missing.

Inactive Ingredients

Almond Oil, Benzyl Alcohol, Benzyl Benzoate, Butylated Hydroxytoluene, Carbomer Copolymer Type B, Cinnamon
Bark Oil, Coriander Oil, Edetate Disodium, Isopropyl Alcohol, L-Arginine HCl, L-Citrulline , Polyoxl 40 Hydrogenated Castor Oil,
Propylene Glycol, Sorbitol,Trolamine, Water